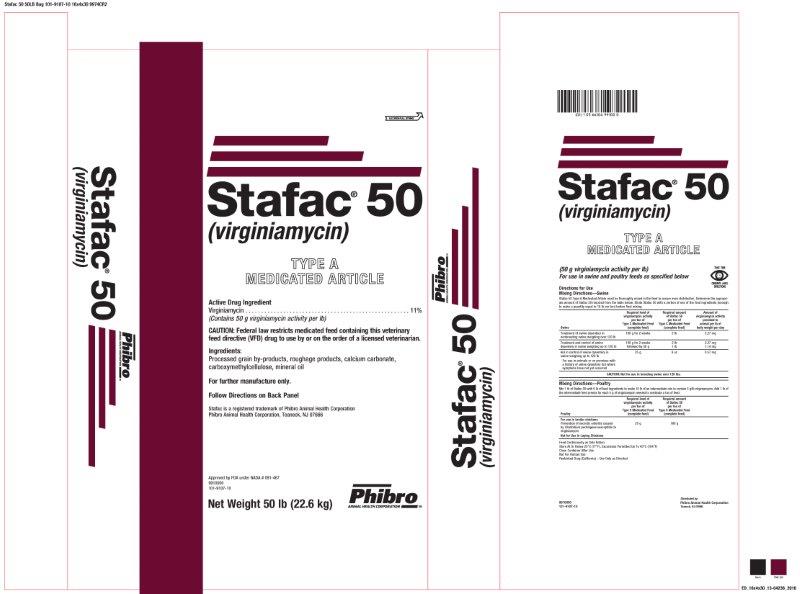 DRUG LABEL: Stafac 50
NDC: 66104-8815 | Form: POWDER
Manufacturer: Phibro Animal Health
Category: animal | Type: VFD TYPE A MEDICATED ARTICLE ANIMAL DRUG LABEL
Date: 20231113

ACTIVE INGREDIENTS: VIRGINIAMYCIN 50 g/0.45 kg
INACTIVE INGREDIENTS: RICE BRAN

Stafac® 50
(virginiamycin)
TYPE A MEDICATED ARTICLE

Active Drug Ingredient

Virginiamycin . . . . . . . . . . . . . . . . . . . . . . . . . . . . . . . . . . . . . . . . 11%

(Contains 50 g virginiamycin activity per lb)

Ingredients:

Processed grain by-products, roughage products, calcium carbonate,

carboxymethylcellulose, mineral oil

Caution:

CAUTION: Federal law restricts medicated feed containing this veterinary feed directive drug to use by or on the order of a licensed veterinarian.

For further manufacture only.

Follow Directions on Back Panel

Stafac is registered trademark of Phibro Animal Health Corporation

Phibro Animal Health Corporation, Teaneck, NJ 07666

Net Weight 50 lb (22.6 kg)

Distributed by:

Phibro Animal Health Corporation

Teaneck, NJ 07666

Approved by FDA under NADA # 091-467

9910000

101-9107-10

INDICATIONS AND USAGE

(50 g virginiamycin activity per lb)

For use in swine and poultry feeds as specified below

Directions for Use

Mixing Directions—Swine

Stafac 50 Type A Medicated Article must be thoroughly mixed in the feed to assure even distribution. Determine the appropriate amount of Stafac 50 required from the table below. Dilute Stafac 50 with a portion of one of the feed ingredients (enough to make a quantity equal to 10 lb per ton) before final mixing.

Swine | Required level of virginiamycin activity per ton of Type C Medicated Feed (complete feed) | Required amount of Stafac 50 per ton of Type C Medicated Feed (complete feed) | Amount of virginiamycin activity provided to animal per lb of body weight per day
Treatment of swine dysentery in nonbreeding swine weighing over 120 lb | 100 g for; 2 weeks | 2 lb | 2.27 mg
Treatment and control of swine dysentery in swine weighing up to 120 lb | 100 g for 2 weeks followed by 50 g | 2 lb; 1 lb | 2.27 mg; 1.14 mg
Aid in control of swine dysentery in swine weighing up to 120 lb; For use in animals or on premises with a history of swine dysentery but where symptoms have not yet occurred | 25 g | 8 oz | 0.57 mg
CAUTION: Not for use in breeding swine over 120 lbs.

Mixing Directions—Poultry

Mix 1 lb of Stafac 50 with 9 lb of feed ingredients to make 10 lb of an intermediate mix to contain 5 g/lb virginiamycin. Add 1 lb of the intermediate feed premix for each 5 g of virginiamycin needed to medicate a ton of feed.

Poultry

Required level of virginiamycin activity per ton of Type C Medicated Feed (complete feed)

Required amount of Stafac 50 per ton of Type C Medicated Feed (complete feed)

For use in broiler chickens

Prevention of necrotic enteritis caused by Clostridium perfringens susceptible to virginiamycin

20 g

180 g

Not for Use in Laying Chickens

Storage and Handling

Feed Continuously as Sole Ration

Store At Or Below 25oC (77oF), Excursions Permitted Up to 40oC (104oF)

Close Container After Use

Not for Human Use

Restricted Drug (California) – Use Only As Directed

Stafac 50